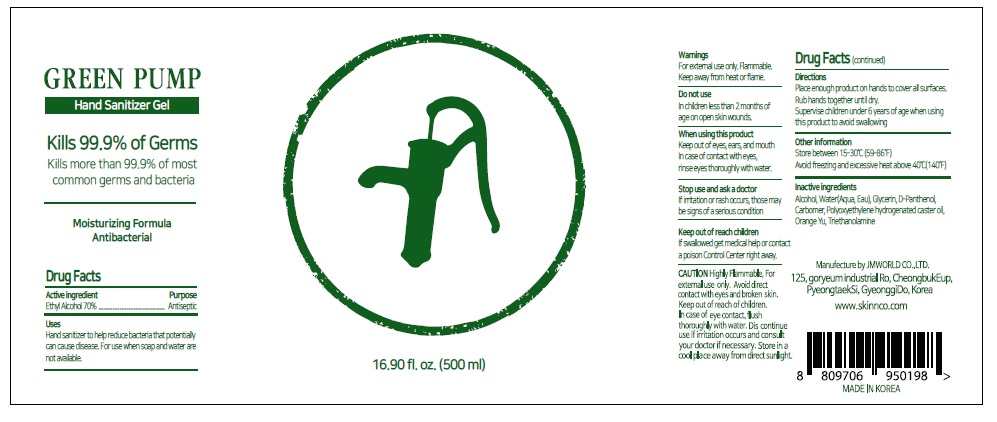 DRUG LABEL: GREEN PUMP
NDC: 81532-001 | Form: GEL
Manufacturer: JM World Co., Ltd.
Category: otc | Type: HUMAN OTC DRUG LABEL
Date: 20210205

ACTIVE INGREDIENTS: ALCOHOL 0.7 mL/1 mL
INACTIVE INGREDIENTS: WATER; GLYCERIN; DEXPANTHENOL; CARBOMER HOMOPOLYMER, UNSPECIFIED TYPE; PEG-10 HYDROGENATED CASTOR OIL; TROLAMINE

81532-001_GREEN PUMP

Active ingredient

Ethyl alcohol 70%

Purpose

Antiseptic

Use

- Hand Sanitizer to help reduce bacteria that potentially can cause disease. For use when soap and water are not available.

Warnings

Flammable. Keep away from fire or flame.

For external use only

When using this product do not use in or near the eyes, ears, and mouth. In case of contact, rinse eyes thoroughly with water.

Stop use and ask a doctor if irritation or rash occurs, those may be signs of a seerious condition.

Keep out of reach of children.

Other information

- Store betweem 15-30°C (59-86°F)
- Avoid freezing and excessive heat above 40°C (140°F)

Directions

Place enough product on hands to cover all surfaces.

Rub hands together until dry.

Supervise children under 6 years of age when using this product to avoid swallowing

Inactive ingredients

Water, Glycerin, D-Panthenol, Carbomer, Polyoxyethylene hydrogenated caster oil, Orange Yu, Triethanolamine